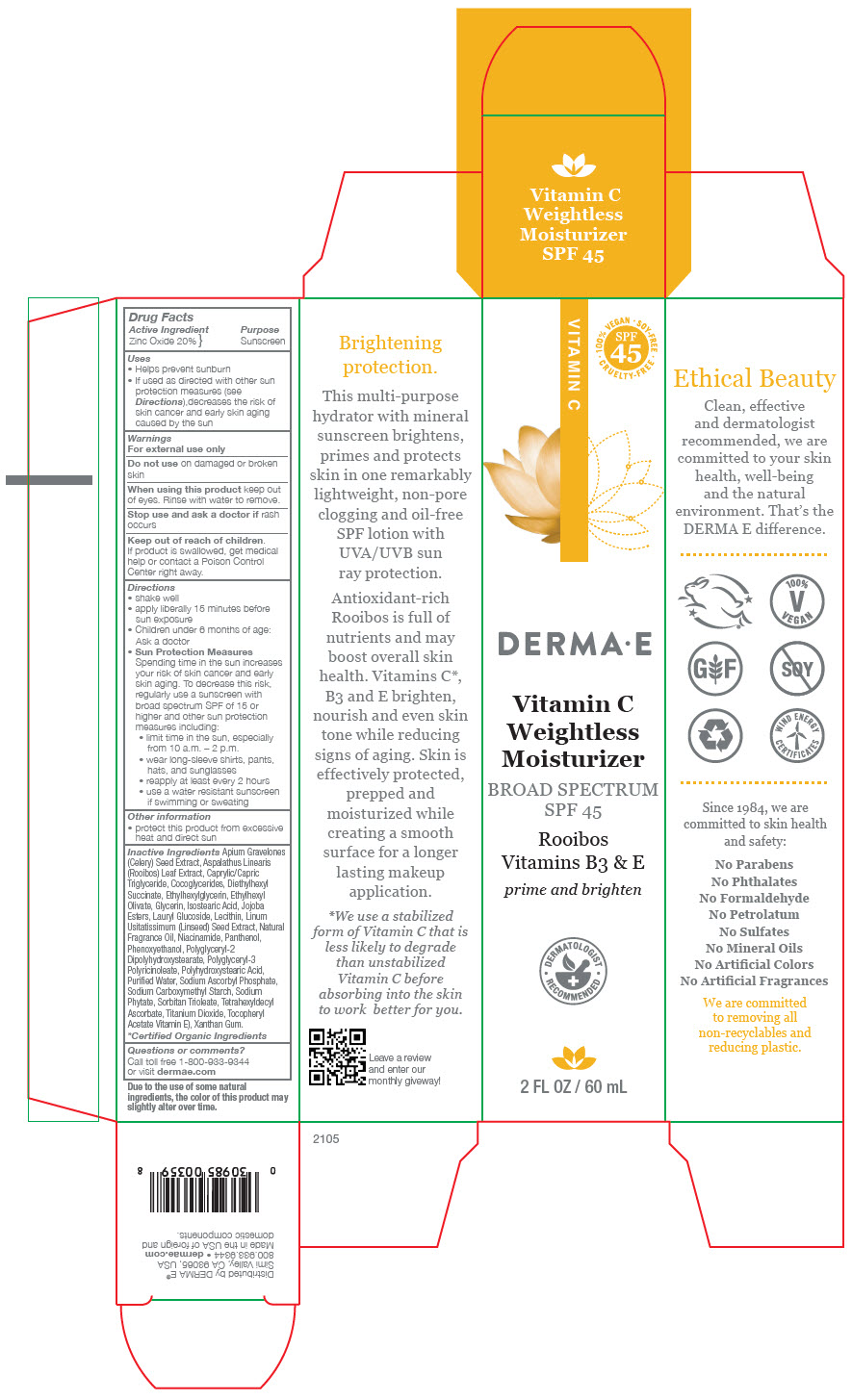 DRUG LABEL: Derma E Vitamin C Weightless Moisturizer 
NDC: 54108-0359 | Form: LOTION
Manufacturer: derma e
Category: otc | Type: HUMAN OTC DRUG LABEL
Date: 20240524

ACTIVE INGREDIENTS: ZINC OXIDE 200 mg/1 mL
INACTIVE INGREDIENTS: WATER; DIETHYLHEXYL SUCCINATE; MEDIUM-CHAIN TRIGLYCERIDES; ETHYLHEXYL OLIVATE; POLYHYDROXYSTEARIC ACID (2300 MW); COCO-GLYCERIDES; GLYCERIN; SODIUM STARCH GLYCOLATE TYPE A; LAURYL GLUCOSIDE; POLYGLYCERYL-2 DIPOLYHYDROXYSTEARATE; PHENOXYETHANOL; .ALPHA.-TOCOPHEROL ACETATE; TETRAHEXYLDECYL ASCORBATE; POLYGLYCERYL-3 PENTARICINOLEATE; ISOSTEARIC ACID; LECITHIN, SUNFLOWER; TITANIUM DIOXIDE; PHYTATE SODIUM; NIACINAMIDE; PANTHENOL; ETHYLHEXYLGLYCERIN; FRAGRANCE 13576; XANTHAN GUM; ASPALATHUS LINEARIS LEAF; SORBITAN TRIOLEATE; HYDROLYZED JOJOBA ESTERS (ACID FORM); SODIUM ASCORBYL PHOSPHATE; CELERY SEED; FLAX SEED

Derma E Vitamin C Weightless Moisturizer
SPF 45

Drug Facts

Active Ingredient

Zinc Oxide 20%

Purpose

Sunscreen

Uses

- Helps prevent sunburn
- If used as directed with other sun protection measures (see Directions),decreases the risk of skin cancer and early skin aging caused by the sun

Warnings

For external use only

Do not use on damaged or broken skin

When using this product keep out of eyes. Rinse with water to remove.

Stop use and ask a doctor if rash occurs

Keep out of reach of children.

If product is swallowed, get medical help or contact a Poison Control Center right away.

Directions

- shake well
- apply liberally 15 minutes before sun exposure
- Children under 6 months of age: Ask a doctor
- Sun Protection Measures Spending time in the sun increases your risk of skin cancer and early skin aging. To decrease this risk, regularly use a sunscreen with broad spectrum SPF of 15 or higher and other sun protection measures including:
  - limit time in the sun, especially from 10 a.m. – 2 p.m.
  - wear long-sleeve shirts, pants, hats, and sunglasses
  - reapply at least every 2 hours
  - use a water resistant sunscreen if swimming or sweating

Other information

- protect this product from excessive heat and direct sun

Inactive Ingredients

Apium Gravelones (Celery) Seed Extract, Aspalathus Linearis (Rooibos) Leaf Extract, Caprylic/Capric Triglyceride, Cocoglycerides, Diethylhexyl Succinate, Ethylhexylglycerin, Ethylhexyl Olivate, Glycerin, Isostearic Acid, Jojoba Esters, Lauryl Glucoside, Lecithin, Linum Usitatissimum (Linseed) Seed Extract, Natural Fragrance Oil, Niacinamide, Panthenol, Phenoxyethanol, Polyglyceryl-2 Dipolyhydroxystearate, Polyglyceryl-3 Polyricinoleate, Polyhydroxystearic Acid, Purified Water, Sodium Ascorbyl Phosphate, Sodium Carboxymethyl Starch, Sodium Phytate, Sorbitan Trioleate, Tetrahexyldecyl Ascorbate, Titanium Dioxide, Tocopheryl Acetate Vitamin E), Xanthan Gum.

*Certified Organic Ingredients

Questions or comments?

Call toll free 1-800-933-9344 or visit dermae.com

Distributed by DERMA E®
Simi Valley, CA 93065, USA

PRINCIPAL DISPLAY PANEL - 60 mL Bottle Box

VITAMIN C

• 100% VEGAN • SOY-FREE •
SPF 45
CRUELTY-FREE

DERMA•E

Vitamin C
Weightless
Moisturizer

BROAD SPECTRUM
SPF 45

Rooibos
Vitamins B3 & E

prime and brighten

• DERMATOLOGIST •
RECOMMENDED

2 FL OZ / 60 mL